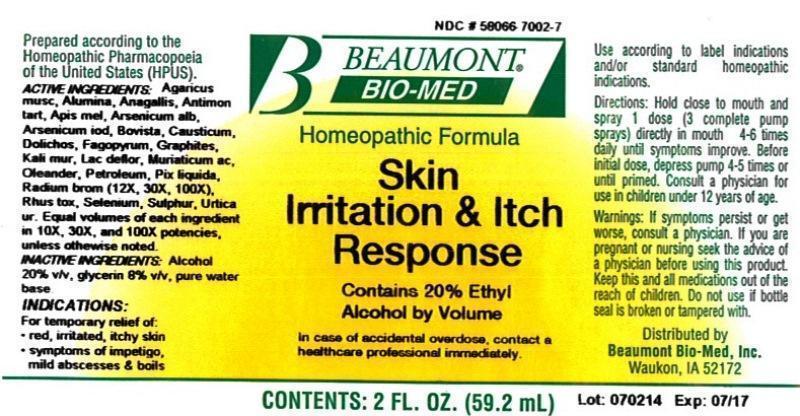 DRUG LABEL: Skin Irritation and Itch Response
NDC: 58066-7002 | Form: LIQUID
Manufacturer: Beaumont Bio Med
Category: homeopathic | Type: HUMAN OTC DRUG LABEL
Date: 20150109

ACTIVE INGREDIENTS: AMANITA MUSCARIA FRUITING BODY 10 [hp_X]/59.2 mL; ALUMINUM OXIDE 10 [hp_X]/59.2 mL; ANAGALLIS ARVENSIS 10 [hp_X]/59.2 mL; ANTIMONY POTASSIUM TARTRATE 10 [hp_X]/59.2 mL; APIS MELLIFERA 10 [hp_X]/59.2 mL; ARSENIC TRIOXIDE 10 [hp_X]/59.2 mL; ARSENIC TRIIODIDE 10 [hp_X]/59.2 mL; LYCOPERDON UTRIFORME FRUITING BODY 10 [hp_X]/59.2 mL; CAUSTICUM 10 [hp_X]/59.2 mL; MUCUNA PRURIENS FRUIT TRICHOME 10 [hp_X]/59.2 mL; FAGOPYRUM ESCULENTUM 10 [hp_X]/59.2 mL; GRAPHITE 10 [hp_X]/59.2 mL; POTASSIUM CHLORIDE 10 [hp_X]/59.2 mL; SKIM MILK 10 [hp_X]/59.2 mL; HYDROCHLORIC ACID 10 [hp_X]/59.2 mL; NERIUM OLEANDER LEAF 10 [hp_X]/59.2 mL; KEROSENE 10 [hp_X]/59.2 mL; PINE TAR 10 [hp_X]/59.2 mL; RADIUM BROMIDE 12 [hp_X]/59.2 mL; TOXICODENDRON PUBESCENS LEAF 10 [hp_X]/59.2 mL; SELENIUM 10 [hp_X]/59.2 mL; SULFUR 10 [hp_X]/59.2 mL; URTICA URENS 10 [hp_X]/59.2 mL
INACTIVE INGREDIENTS: ALCOHOL; GLYCERIN; WATER

Skin Irritation and Itch Response

ACTIVE INGREDIENT

HPUS active ingredients: Agaricus muscarius, Alumina, Anagallis arvensis, Antimonium tartaricum, Apis mellifica, Arsenicum album, Arsenicum iodatum, Bovista, Causticum, Dolichos pruriens, Fagopyrum esculentum, Graphites, Kali muriaticum, Lac defloratum, Muriaticum acidum, Oleander, Petroleum, Pix Liquida, Radium bromatum (12X, 30X, 100X), Rhus toxicodendron, Selenium metallicum, Sulphur, Urtica urens. Equal volumes of each ingredient in 10X, 30X, 100X potencies, unless otherwise noted.

INACTIVE INGREDIENT

Inactive Ingredients: Alcohol @ 20% v/v, Glycerin @ 8% v/v, in a pure water base.

INDICATIONS AND USAGE

Indications: For temporary relief of: red, irritated, itchy skin, symptoms of impetigo, mild abscesses and boils.

Directions:

- Hold close to mouth and spray 1 dose (3 complete pump sprays) directly in mouth 4-6 times daily until symptoms improve.
- Before initial dose, depress pump 4-5 times or until primed.
- Consult a physician for use in children under 12 years of age.

Use according to label indications and/or standard homeopathic indications.

WARNINGS

Warnings: If symptoms persist or get worse, consult a physician. If you are pregnant or nursing seek the advice of a physician before using this product. Keep this and all medications out of the reach of children. Do not use if bottle seal is broken or tampered with.

- Keep out of reach of children.

PURPOSE

For temporary relief of:

- red, irritated, itchy skin
- symptoms of impetigo, mild abscesses and boils